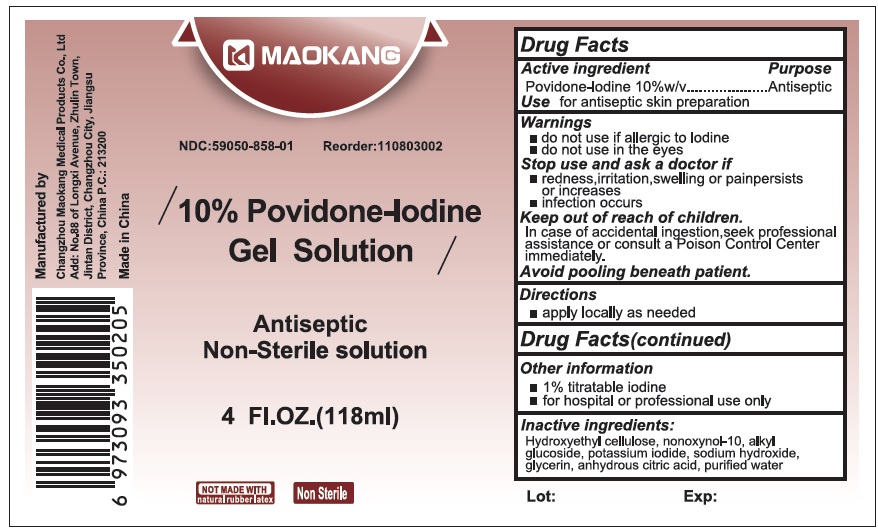 DRUG LABEL: Maokang Povidone-Iodine Antiseptic
NDC: 59050-858 | Form: LIQUID
Manufacturer: Changzhou Maokang Medical Products Co
Category: otc | Type: HUMAN OTC DRUG LABEL
Date: 20260223

ACTIVE INGREDIENTS: POVIDONE-IODINE 100 mg/1 mL
INACTIVE INGREDIENTS: HYDROXYETHYL CELLULOSE, UNSPECIFIED; NONOXYNOL-10; POTASSIUM IODIDE; SODIUM HYDROXIDE; GLYCERIN; ANHYDROUS CITRIC ACID; WATER

Maokang Povidone-Iodine Antiseptic

Active ingredient

Povidone-lodine 10%

Purpose

Antiseptic

Use

for antiseptic skin preparation

Warnings

• do not use if allergic to Iodine
• do not use in the eyes

Stop use and ask a doctor if

• redness,irritation,swelling or painpersists or Increases
• infection occurs

Keep out of reach of children.

In case of accidental incestion,seek professional assistance or consult a poison Control Center immediately.

Avoid pooling beneath patient.

Directions

• apply locally as needed

Other information

- 1% titratable iodine
- for hospital or professional use only

Inactive ingredients:

Hydroxyethyl cellulose, nonoxynol-10, alkyl glucoside, potassium iodide, sodium hydroxide, glycerin, anhydrous citric acid, purified water